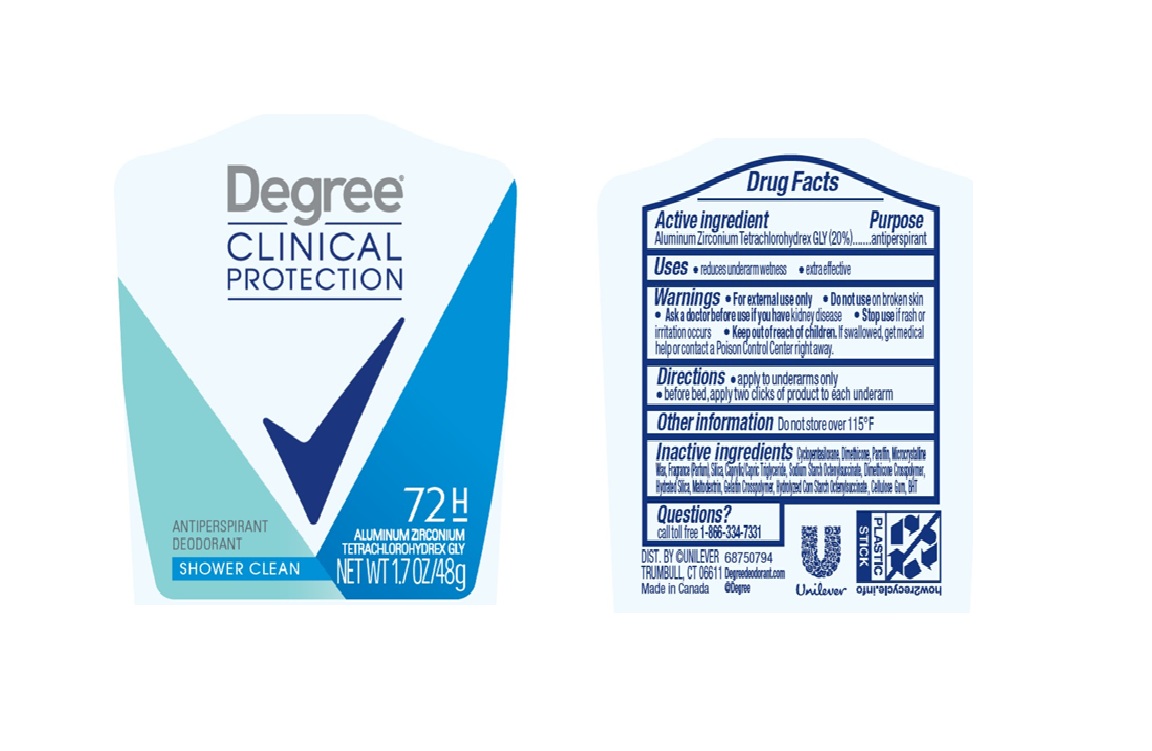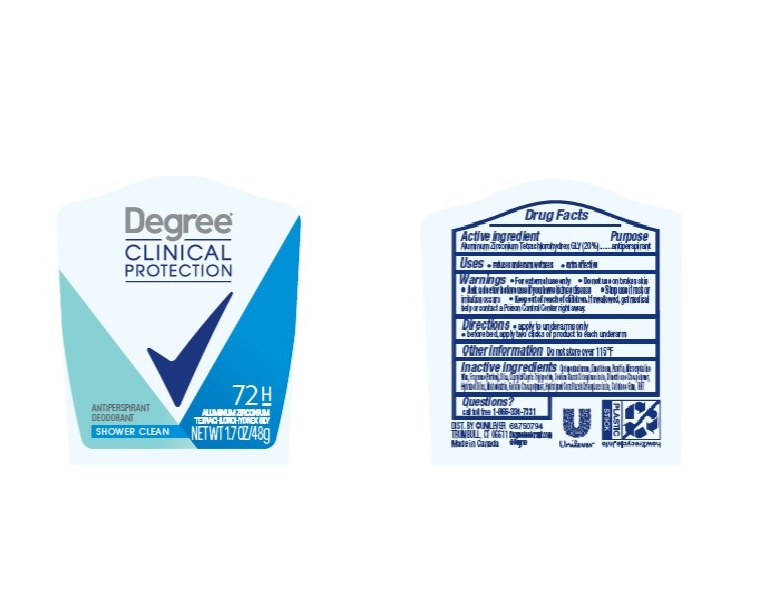 DRUG LABEL: Degree
NDC: 64942-1304 | Form: STICK
Manufacturer: Conopco Inc. d/b/a Unilever
Category: otc | Type: HUMAN OTC DRUG LABEL
Date: 20260226

ACTIVE INGREDIENTS: ALUMINUM ZIRCONIUM TETRACHLOROHYDREX GLY 20 g/100 g
INACTIVE INGREDIENTS: DIMETHICONE; MICROCRYSTALLINE WAX; SILICON DIOXIDE; HYDRATED SILICA; MALTODEXTRIN; STARCH, CORN; GELATIN; CARBOXYMETHYLCELLULOSE SODIUM; BUTYLATED HYDROXYTOLUENE; PARAFFIN; CYCLOMETHICONE 5

Degree Clinical Protection Shower Clean 72H Antiperspirant Deodorant

Active Ingredient

Aluminum Zirconium Tetrachlorohydrex GLY (20%)

Purpose
anti-perspirant

Warnings
For external use only

Do not use on broken skin

Ask a doctor before use if you have kidney disease

Stop use if rash or irritation occurs

Keep out of reach of children. If swallowed, get medical help or contact a Poison Control Center right away.

Uses
▪ reduces underarm wetness
▪ extra effective

Directions
▪ apply to underarms only
▪ before bed, apply two clicks of product to each underarm

Inactive ingredients
Cyclopentasiloxane
Dimethicone
Paraffin
Microcrystalline Wax
Fragrance (Parfum)
Silica
Caprylic/Capric Triglyceride
Sodium Starch Octenylsuccinate
Dimethicone Crosspolymer
Hydrated silica
Maltodextrin
Gelatin crosspolymer
Hydrolyzed Corn Starch
Cellulose Gum
BHT

Questions? Call toll-free 1-866-334-7331